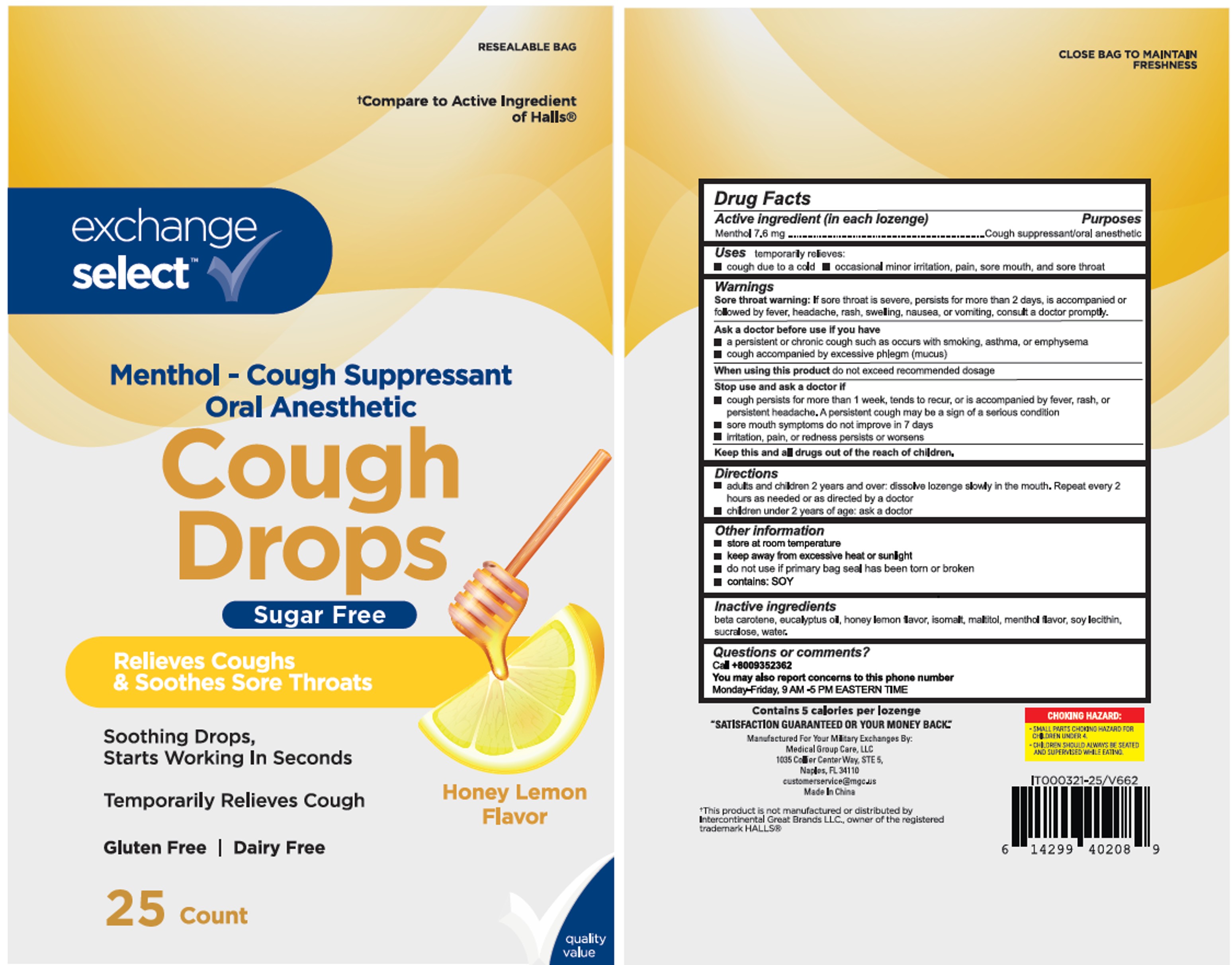 DRUG LABEL: Exchange Select Cough Drops
NDC: 83698-583 | Form: LOZENGE
Manufacturer: Xiamen Kang Zhongyuan Biotechnology Co., Ltd.
Category: otc | Type: HUMAN OTC DRUG LABEL
Date: 20250620

ACTIVE INGREDIENTS: MENTHOL 7.6 mg/1 1
INACTIVE INGREDIENTS: SUCRALOSE; WATER; BETA CAROTENE; LECITHIN, SOYBEAN; ISOMALT; EUCALYPTUS OIL; MALTITOL

MGC-YNBY Cough Drops Honey Sugar-Free 25, 70

Active Ingredient(s)

Menthol 7.6 mg

Purpose

Purposes cough suppressant, oral anesthetic

Use

temporary relieves: ■ cough due to cold ■ occasional minor irritation, pain, sore mouth, and sore throat

Warnings

Sore throat warning: If sore throat is severe, persists more than 2 days, or is accompanied by fever, headache, rash, swelling, nausea, or vomiting, consult a doctor promptly.

Ask a doctor before use if you have: ■ persistent or chronic cough such as occurs with smoking, asthma, or emphysema ■ cough accompanied by excessive phlegm (mucus).

When using this product:
Do not exceed recommended dosage.

Stop use and ask a doctor if ■ cough persists for more than 1 week, tends to recur, or is accompained by fever, rash, or persistent headache. ■ sore mouth does not improve in 7 days ■ irritation, pain, or redness persists or worsens.

Keep out of reach of children.

Directions

- Adults and children 2 years and over: dissolve lozenge slowly in mouth. Repeat every 2 hours as needed or as directed by a doctor.
- Children under 2 years: ask a doctor.

Other information

- Store at room temperature
- Keep away from excessive heat or sunlight
- Do not use if primary bag seal is torn or broken
- Contains: SOY

Inactive ingredients

beta carotene, eucalyptus oil, honey lemon flavor, isomalt, maltitol, menthol flavor, soy lecithin, sucralose, water.

QUESTIONS

Call +8009352362
Available Monday–Friday, 9 AM–5 PM Eastern Time